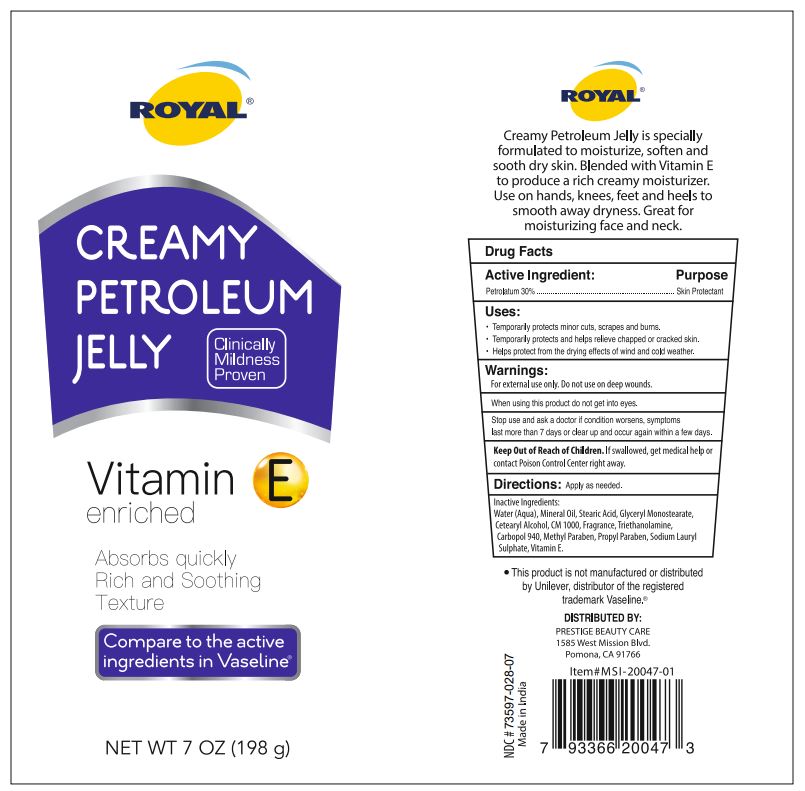 DRUG LABEL: Royal Creamy Petroleum Jelly
NDC: 73597-028 | Form: JELLY
Manufacturer: Mission Series Inc. dba Prestige Beauty Care
Category: otc | Type: HUMAN OTC DRUG LABEL
Date: 20250709

ACTIVE INGREDIENTS: PETROLATUM 30 g/100 g
INACTIVE INGREDIENTS: GLYCERYL MONOSTEARATE; .ALPHA.-TOCOPHEROL; WATER; CETOSTEARYL ALCOHOL; PROPYLPARABEN; SODIUM LAURYL SULFATE; CETETH-20; MINERAL OIL; STEARIC ACID; TROLAMINE; CARBOMER 940; METHYLPARABEN

Royal Creamy Petroleum Jelly

Active Ingredient

Active Ingredient: Petrolatum 30%

Purpose

Purpose Skin Protectant

Indications & Usage

Uses:

Temporarily protects minor cuts, scrapes, and burns.

Temporarily protects and helps relieve chapped or cracked skin.

Helps protect from the drying effects of wind and cold weather.

Warnings

For external use only. Do not use on deep wounds.

When using this product do not get into eyes.

Stop Use

Stop use and ask a doctor if condition worsens, symptoms last more than 7 days or clear up and occur again within a few days.

Keep Out of Reach of Children. If swallowed, get medical help or contact Poison Control Center right away.

Directions

Directions: Apply as needed.

Inactive Ingredients

Water (Aqua), Mineral Oil, Stearic Acid, Glyceryl Monostearate, Cetearyl Alcohol, CM 1000, Fragrance, Triethanolamine, Carbopol 940, Methyl Paraben, Propyl Paraben, Sodium Lauryl Sulphate, Vitamin E.

Made in India

DISTRIBUTED BY:

PRESTIGE BEAUTY CARE

1585 West Mission Blvd.

Pomona, CA 91766

*This product is not manufactured or distributed by Unilever, distributor of the registered trademark Vaseline(r)

Creamy Petroleum Jelly is specially formulated to moisturize, soften and sooth dry skin. Blended with Vitamin E to produce a rich creamy moisturizer. Use on hands, knees, feet and heels to smooth away dryness. Great for moisturizing face and neck.